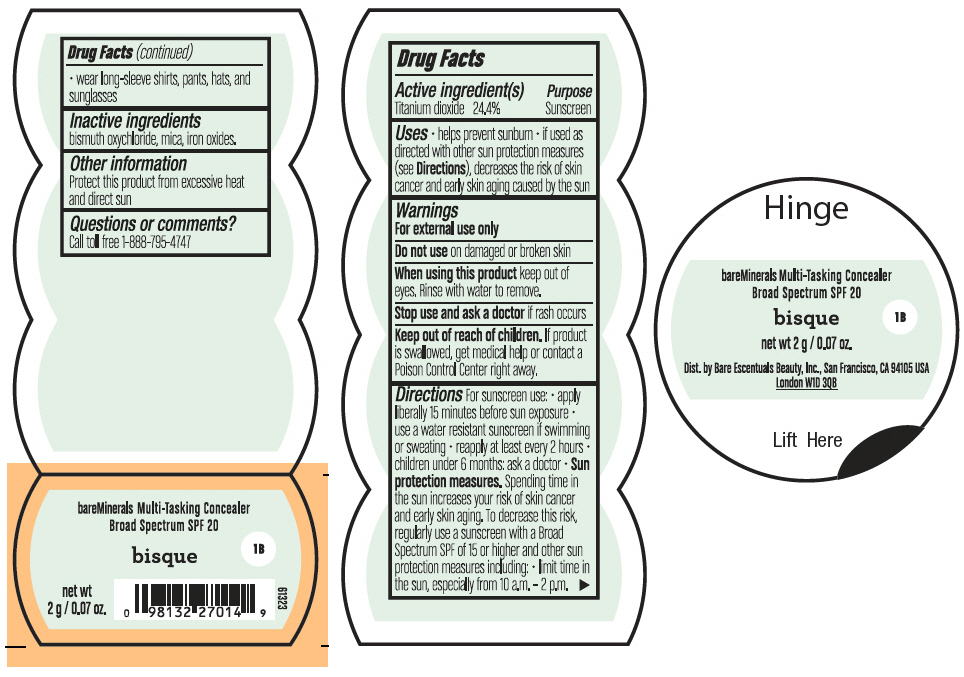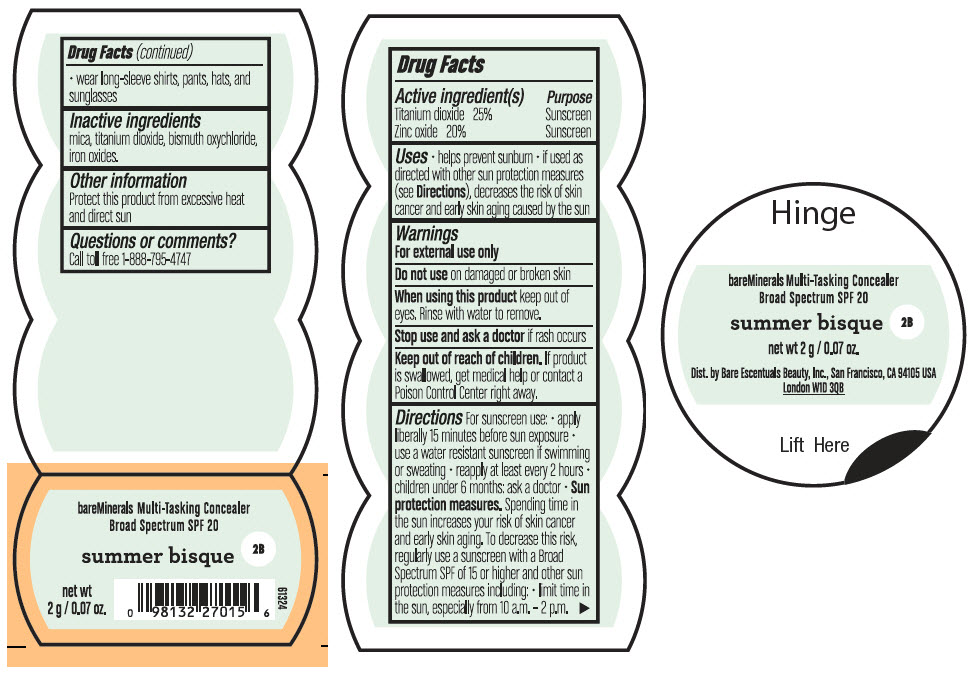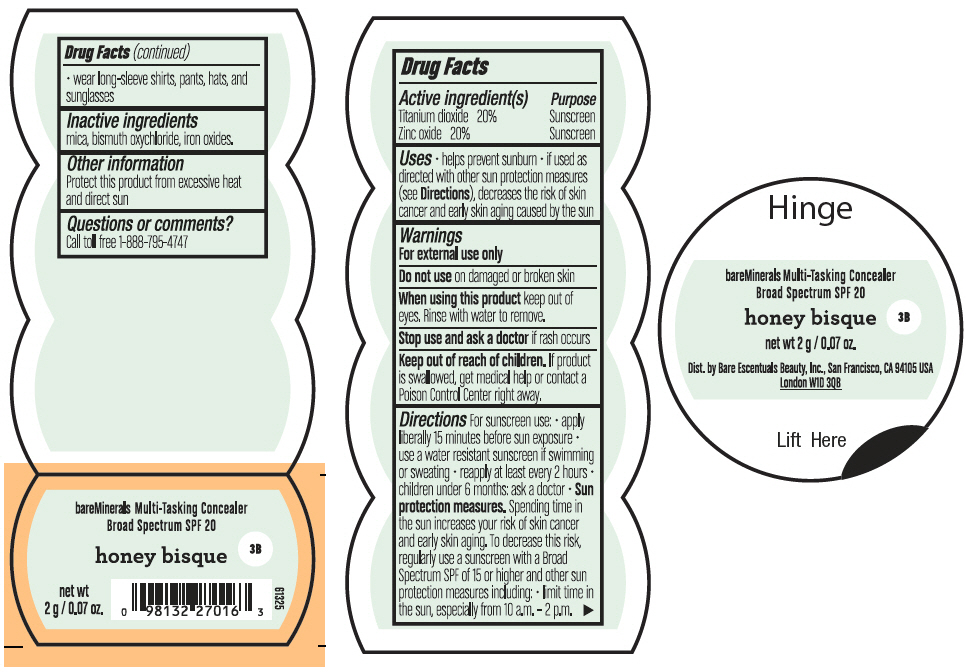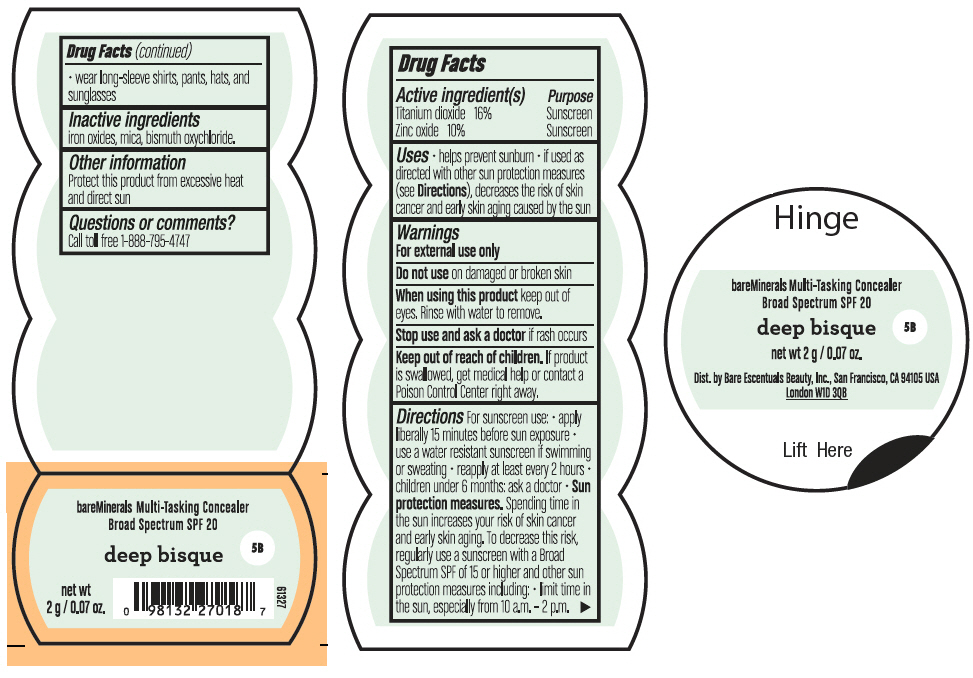 DRUG LABEL: bareMinerals Multi-Tasking SPF 20 Concealer
NDC: 98132-005 | Form: POWDER
Manufacturer: Orveon Global US LLC
Category: otc | Type: HUMAN OTC DRUG LABEL
Date: 20231004

ACTIVE INGREDIENTS: TITANIUM DIOXIDE 488 mg/2 g
INACTIVE INGREDIENTS: BISMUTH OXYCHLORIDE; MICA; FERRIC OXIDE RED

bareMinerals Multi-Tasking SPF 20 Concealer

Drug Facts

Active ingredients

Titanium Dioxide 24.4%

Purpose

Sunscreen

Uses

- helps prevent sunburn
- if used as directed with other sun protection measures (see Directions), decreases the risk of skin cancer and early skin aging caused by the sun

Warnings

- For external use only

- Do not use on damaged or broken skin

- When using this product keep out of eyes. Rinse with water to remove

- Stop use and ask a doctor if rash occurs

- Keep out of reach of children. If product is swallowed, get medical help or contact a Poison Control Center right away

Directions

For sunscreen use:

- Apply liberally 15 minutes before sun exposure
- Use a water-resistant sunscreen if swimming or sweating
- Reapply at least every 2 hours
- Children under 6 months: ask a doctor
- Sun Protection Measures. Spending time in the sun increases your risk of skin cancer and early skin aging. To decrease this risk, regularly use a sunscreen with a Broad Spectrum SPF of 15 or higher and other sun protection measures including:
  - limit time in the sun, especially from 10 a.m. – 2 p.m.
  - wear long-sleeve shirts, pants, hats, and sunglasses

Inactive Ingredients

bismuth oxychloride, mica, iron oxides.

Other information

Protect this product from excessive heat and direct sun

Questions or comments?

Call toll free 1-888-795-4747

Dist. by Bare Escentuals Beauty, Inc., San Francisco, CA 94105 USA

PRINCIPAL DISPLAY PANEL - 2 g Jar Label - Bisque

bareMinerals Multi-Tasking Concealer
Broad Spectrum SPF 20

bisque

1B

net wt
2 g / 0.07 oz.

61323

PRINCIPAL DISPLAY PANEL - 2 g Jar Label - Summer Bisque

bareMinerals Multi-Tasking Concealer
Broad Spectrum SPF 20

summer bisque

2B

net wt
2 g / 0.07 oz.

61324

PRINCIPAL DISPLAY PANEL - 2 g Jar Label - Honey Bisque

bareMinerals Multi-Tasking Concealer
Broad Spectrum SPF 20

honey bisque

3B

net wt
2 g / 0.07 oz.

61325

PRINCIPAL DISPLAY PANEL - 2 g Jar Label - Deep Bisque

bareMinerals Multi-Tasking Concealer
Broad Spectrum SPF 20

deep bisque

5B

net wt
2 g / 0.07 oz.

61327